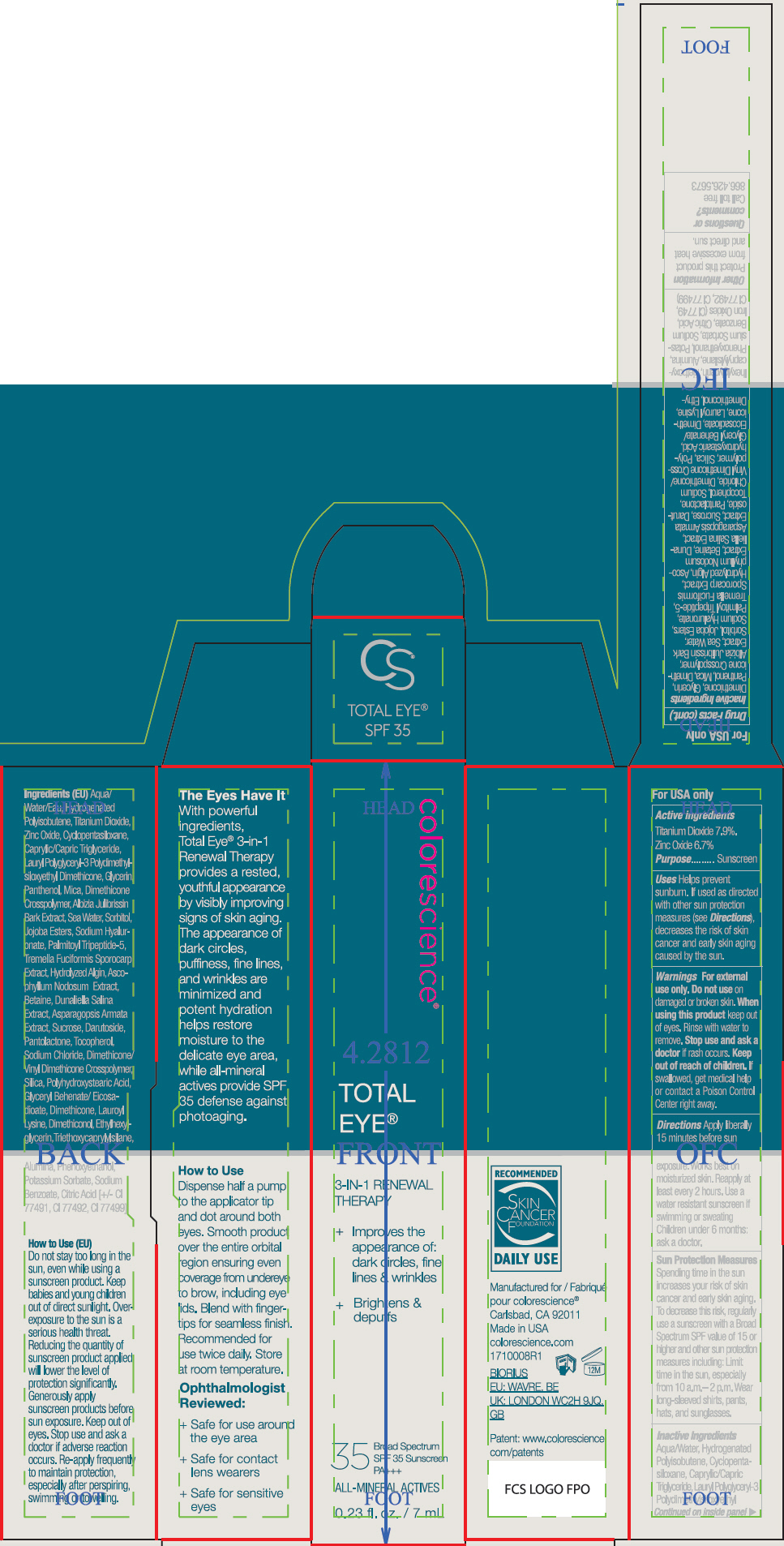 DRUG LABEL: Total Eye 3-In-1 Renewal Therapy SPF 35
NDC: 68078-024 | Form: LIQUID
Manufacturer: Colorescience
Category: otc | Type: HUMAN OTC DRUG LABEL
Date: 20251216

ACTIVE INGREDIENTS: TITANIUM DIOXIDE 79 mg/1 mL; ZINC OXIDE 67 mg/1 mL
INACTIVE INGREDIENTS: WATER; HYDROGENATED POLYISOBUTENE (1300 MW); CYCLOMETHICONE 5; MEDIUM-CHAIN TRIGLYCERIDES; GLYCERIN; PANTHENOL; MICA; DIMETHICONE CROSSPOLYMER; ALBIZIA JULIBRISSIN BARK; JOJOBA OIL, RANDOMIZED; HYALURONATE SODIUM; PALMITOYL TRIPEPTIDE-5; ASCOPHYLLUM NODOSUM; BETAINE; DUNALIELLA SALINA; ASPARAGOPSIS ARMATA; SUCROSE; DARUTOSIDE; TOCOPHEROL; SODIUM CHLORIDE; DIMETHICONE/VINYL DIMETHICONE CROSSPOLYMER (SOFT PARTICLE); SILICON DIOXIDE; POLYHYDROXYSTEARIC ACID STEARATE; GLYCERYL BEHENATE/EICOSADIOATE; DIMETHICONE, UNSPECIFIED; LAUROYL LYSINE; ETHYLHEXYLGLYCERIN; TRIETHOXYCAPRYLYLSILANE; ALUMINUM OXIDE; PHENOXYETHANOL; POTASSIUM SORBATE; SODIUM BENZOATE; CITRIC ACID MONOHYDRATE; PENTYLENE GLYCOL; HYDROGENATED STARCH HYDROLYSATE; LAURYL POLYGLYCERYL-3 POLYDIMETHYLSILOXYETHYL DIMETHICONE (4000 MPA.S); TREMELLA FUCIFORMIS FRUITING BODY; FERRIC OXIDE RED; FERRIC OXIDE YELLOW; FERROSOFERRIC OXIDE; ALGINIC ACID

Total Eye™ 3-In-1 Renewal Therapy SPF 35

Drug Facts

ACTIVE INGREDIENT

Active ingredients | Purpose
Titanium Dioxide 7.9% | Sunscreen
Zinc Oxide 6.7% | Sunscreen

Uses

- Helps prevent sunburn.
- If used as directed with other sun protection measures (see Directions), decreases the risk of skin cancer and early skin aging caused by the sun.

Warnings

For external use only. Do not use on damaged or broken skin. When using this product keep out of eyes. Rinse with water to remove. Stop use and ask a doctor if rash occurs.

Keep out of reach of children.If swallowed, get medical help or contact a Poison Control Center right away.

Directions

- Apply liberally 15 minutes before sun exposure. Works best on moisturized skin.
- Reapply at least every 2 hours
- Use a water resistant sunscreen if swimming or sweating
- Children under 6 months: ask a doctor.

Sun Protection Measures

Spending time in the sun increases your risk of skin cancer and early skin aging. To decrease this risk, regularly use a sunscreen with a Broad Spectrum SPF value of 15 or higher and other sun protection measures including:

- Limit time in the sun, especially from 10 a.m.– 2 p.m.
- Wear long-sleeved shirts, pants, hats, and sunglasses.

Inactive Ingredients

Aqua/Water, Hydrogenated Polyisobutene, Cyclopentasiloxane, Caprylic/Capric Triglyceride, Lauryl Polyglyceryl-3 Polydimethylsiloxyethyl Dimethicone, Glycerin, Panthenol, Mica, Dimethicone Crosspolymer, Albizia Julibrissin Bark Extract, Sea Water, Sorbitol, Jojoba Esters, Sodium Hyaluronate, Palmitoyl Tripeptide-5, Tremella Fuciformis Sporocarp Extract, Hydrolyzed Algin, Ascophyllum Nodosum Extract, Betaine, Dunaliella Salina Extract, Asparagopsis Armata Extract, Sucrose, Darutoside, Pantolactone, Tocopherol, Sodium Chloride, Dimethicone/Vinyl Dimethicone Crosspolymer, Silica, Polyhydroxystearic Acid, Glyceryl Behenate/Eicosadioate, Dimethicone, Lauroyl Lysine, Dimethiconol, Ethylhexylglycerin, Triethoxycaprylylsilane, Alumina, Phenoxyethanol, Potassium Sorbate, Sodium Benzoate, Citric Acid, Iron Oxides (CI 77491, CI 77492, CI 77499)

Other Information

Protect this product from excessive heat and direct sun.

Questions or comments?

Call toll free 866.426.5673

Dist. in USA by colorescience®
Carlsbad, CA 92011

PRINCIPAL DISPLAY PANEL - 7 mL Tube Carton

colorescience®

TOTAL
EYE®

3-IN-1 RENEWAL
THERAPY

+ Improves the
  appearance of:
  dark circles, fine
  lines & wrinkles
+ Brightens &
  depuffs

35
Broad Spectrum
SPF 35 Sunscreen
PA+++

ALL-MINERAL ACTIVES

0.23 fl. oz. / 7 mL

PRINCIPAL DISPLAY PANEL - 7 mL Tube Carton - Fair

colorescience®

TOTAL
EYE®

3-IN-1 RENEWAL
THERAPY

+ Improves the
  appearance of:
  dark circles, fine
  lines & wrinkles
+ Brightens &
  depuffs

35
Broad Spectrum
SPF 35 Sunscreen
PA+++

ALL-MINERAL ACTIVES

0.23 fl. oz. / 7 mL

PRINCIPAL DISPLAY PANEL - 7 mL Tube Carton - Tan

colorescience®

TOTAL
EYE®

3-IN-1 RENEWAL
THERAPY

+ Improves the
  appearance of:
  dark circles, fine
  lines & wrinkles
+ Brightens &
  depuffs

35
Broad Spectrum
SPF 35 Sunscreen
PA+++

ALL-MINERAL ACTIVES

0.23 fl. oz. / 7 mL

PRINCIPAL DISPLAY PANEL - 7 mL Tube Carton - Deep

colorescience®

TOTAL
EYE®

3-IN-1 RENEWAL
THERAPY

+ Improves the
  appearance of:
  dark circles, fine
  lines & wrinkles
+ Brightens &
  depuffs

35
Broad Spectrum
SPF 35 Sunscreen
PA+++

ALL-MINERAL ACTIVES

0.23 fl. oz. / 7 mL